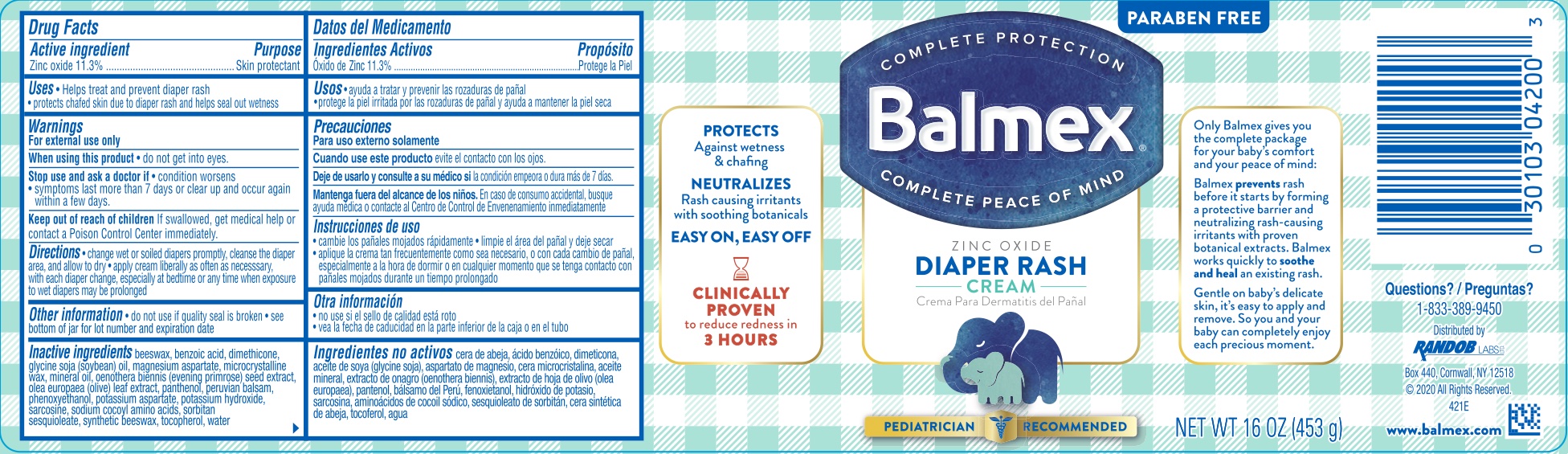 DRUG LABEL: Balmex Diaper Rash
NDC: 52412-285 | Form: CREAM
Manufacturer: Randob Labs, LTD
Category: otc | Type: HUMAN OTC DRUG LABEL
Date: 20241215

ACTIVE INGREDIENTS: ZINC OXIDE 11.3 g/100 g
INACTIVE INGREDIENTS: BENZOIC ACID; DIMETHICONE 350; SOYBEAN OIL; MAGNESIUM ASPARTATE; MICROCRYSTALLINE WAX; MINERAL OIL; EVENING PRIMROSE OIL; OLEA EUROPAEA LEAF; PANTHENOL; BALSAM PERU; PHENOXYETHANOL; POTASSIUM ASPARTATE; POTASSIUM HYDROXIDE; SARCOSINE; COCO ACID CHLORIDES; SORBITAN SESQUIOLEATE; SYNTHETIC BEESWAX; TOCOPHEROL; WATER; YELLOW WAX

Balmex Diaper Rash Cream

ACTIVE INGREDIENT

Zinc Oxide 11.3%

PURPOSE

Skin Protectant

INDICATIONS AND USAGE

Helps treat and prevent diaper rash, protects chafed skin due to diaper rash and helps seal out wetness.

WARNINGS

For external use only.

When using this product do not get into eyes.

Stop use and ask a doctor if condition worsens, symptoms last more than 7 days or clear up and occur again within a few days.

KEEP OUT OF REACH OF CHILDREN

If swallowed, seek medical help or contact a Poison Control Center immediately.

DOSAGE AND ADMINISTRATION

Change wet and soiled diapers promptly, cleanse the diaper area, and allow to dry. Apply cream liberally as often as necessary, with each diaper change, especially at bedtime or anytime when exposure to wet diapers may be prolonged.

INACTIVE INGREDIENT

Beeswax, benzoic acid, dimethicone, glycine soja (soybean) oil, magnesium aspartate, microcrystalline wax, mineral oil, oenothera biennis (evening primrose) seed extract, olea europae (olive) leaf extract, panthenol, Peruvian balsam, Phenoxyethanol, potassium aspartate, potassium hydroxide, sarcosine, sodium cocoyl amino acids, sorbitan sesquioleate, synthetic beeswax, tocopherol, water.